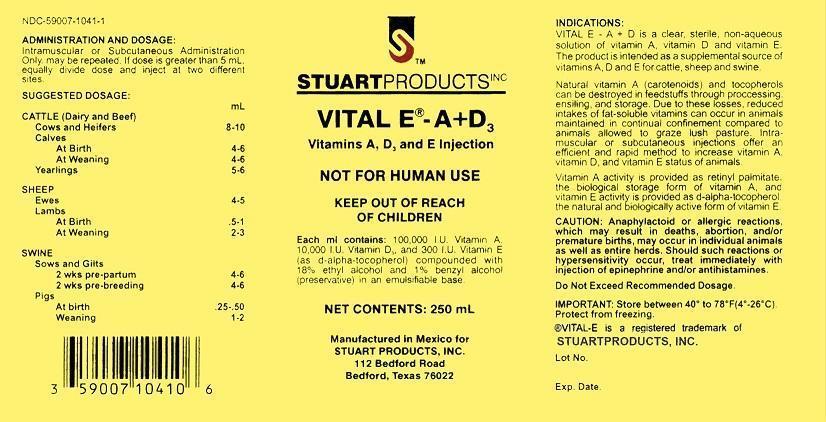 DRUG LABEL: Vital E -
NDC: 59007-1041 | Form: INJECTION, EMULSION
Manufacturer: Stuart Products, Inc.
Category: animal | Type: OTC ANIMAL DRUG LABEL
Date: 20151009

ACTIVE INGREDIENTS: ALPHA-TOCOPHEROL, D- 300 [iU]/1 mL; VITAMIN A PALMITATE 100000 [iU]/1 mL; CHOLECALCIFEROL 10000 [iU]/1 mL
INACTIVE INGREDIENTS: ALCOHOL 180 1/1 mL; BENZYL ALCOHOL 10 1/1 mL

INDICATIONS:

VITAL E–A+D3 is a clear, sterile, non-aqueous solution of vitamins A, Vitamin D and Vitamin E. The product is intended as a supplemental source of vitamin A, vitamin D and vitamin E for cattle, sheep, and swine.

Natural Vitamin A (carotenoids) and tocopherols can be destroyed in feedstuffs through processing, ensiling, and storage. Due to those losses reduced intakes of fat-soluble vitamins can in animals maintained in continual confinement compared top animals allowed to graze lush pasture. Intramuscular or subcutaneous injections offer an efficient and rapid method to increase vitamin A, vitamin D, and vitamin E status of the animals.

Vitamin A activity is provided as retinyl palmitate, the biological storage form of vitamin A and vitamin E activity is provided as d-alpha-tocopherol, the natural and biologically active form of vitamin E.

ADMINISTRATION AND DOSAGE:

Intramuscular or Subcutaneous Adminstration Only, may be repeated. If dose is greater than 5 mL, equally divide dose and inject at two different sites.

SUGGESTED DOSAGE:

CATTLE (Dairy and Beef)

Cows and Heifers 8-10 mL

Calves

At Birth 4-6 mL

At Weaning 4-6 mL

Yearlings 5-6 mL

SHEEP

Ewes 4-5 mL

Lambs

At Birth: .5-1 mL

At Weaning 2-3 mL

SWINE

Sows and Gilts

2 wks pre-partum 4-6 mL

2 wks pre-breeding 4-6 mL

Pigs

At births .25-.50 mL

Weaning: 1-2 mL

PRECAUTIONS

CAUTION: Anaphylactoid or allergic reactions, which may result in deaths, abortion, and/or premature births, may occur in individual animals as well as entire herds. Should such reactions or hypersensitivity occur, treat immediately with injection of epinephrine and/or antihistamines.

Do Not Exceed Recommended Dosage.

STORAGE AND HANDLING

IMPORTANT: Stored between 40° to 78° F (4°-26°C). Protect from freezing.

®VITAL-E is a registered trademark of

STUARTPRODUCTS, INC.

Principal Display Panel - 250 mL Bottle

STUART PRODUCTS INC

VITAL E® - A+D3

Vitamin A, D and E Injection

NOT FOR HUMAN USE

KEEP OUT OF REACH OF CHILDREN

Each ml contains: 100,000 I.U. Vitamin A, 10,000 I.U. Vitamin D and 300 I.U. vitamin E (as d-alpha-tocopherol) compounded with 18% ethyl alcohol and 1% benzyl alcohol (preservative) in an emulsifiable base.

NET CONTENTS: 250 mL

Manufactured in Mexico for

STUART PRODUCTS, INC.

112 Bedford Road

Bedford, Texas 76022